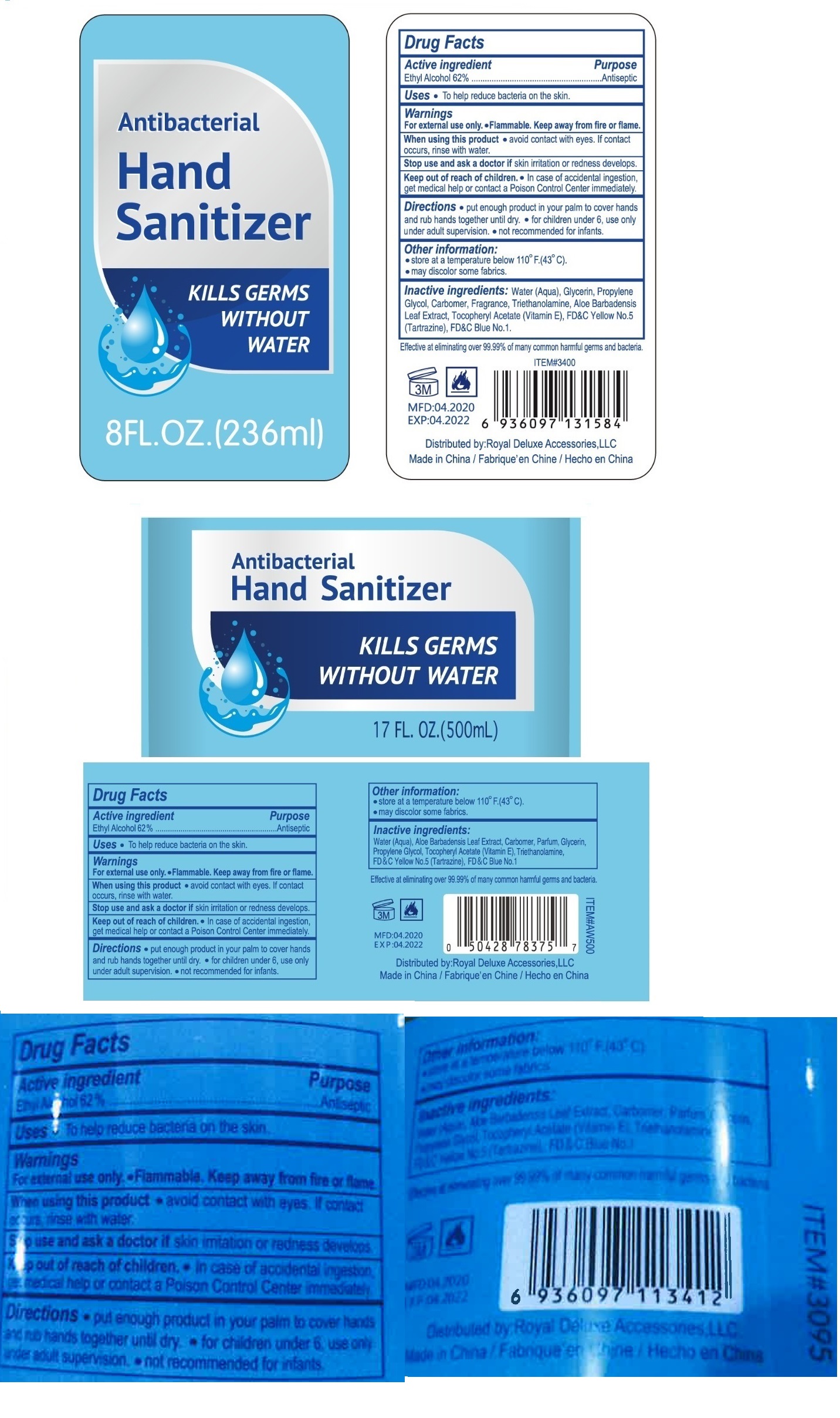 DRUG LABEL: Antibacterial Hand Sanitizer
NDC: 77043-166 | Form: LIQUID
Manufacturer: Royal Deluxe Accessories Llc
Category: otc | Type: HUMAN OTC DRUG LABEL
Date: 20200428

ACTIVE INGREDIENTS: ALCOHOL 62 mL/100 mL
INACTIVE INGREDIENTS: WATER; GLYCERIN; PROPYLENE GLYCOL; CARBOMER HOMOPOLYMER, UNSPECIFIED TYPE; TROLAMINE; ALOE VERA LEAF; .ALPHA.-TOCOPHEROL ACETATE; FD&C YELLOW NO. 5; FD&C BLUE NO. 1

Antibacterial Hand Sanitizer

Active ingredient

Ethyl Alcohol 62%

Purpose

Antiseptic

Uses

• To help reduce bacteria on the skin.

Warnings

For external use only. •Flammable. Keep away from fire or flame.

When using this product • avoid contact with eyes. If contact occurs, rinse with water.

Stop use and ask a doctor if skin irritation or redness develops.

Keep out of reach of children. • In case of accidental ingestion, get medical help or contact a Poison Control Center immediately.

Directions

• put enough product in your palm to cover hands and rub hands together until dry. • for children under 6, use only under adult supervision.

• not recommended for infants.

Other information:

- store at a temperature below 110°F.(43°C).
- may discolor some fabrics.

Inactive ingredients:

Water (Aqua), Glycerin, Propylene Glycol, Carbomer, Fragrance, Triethanolamine, Aloe Barbadensis Leaf Extract, Tocopheryl Acetate (Vitamin E), FD&C Yellow No.5 (Tartrazine), FD&C Blue No.1.

KILLS GERMS WITHOUT WATER

Effective at eliminating over 99.99% of many common harmful germs and bacteria.

Distributed by:Royal Deluxe Accessories,LLC

Made in China / Fabrique'en Chine / Hecho en China